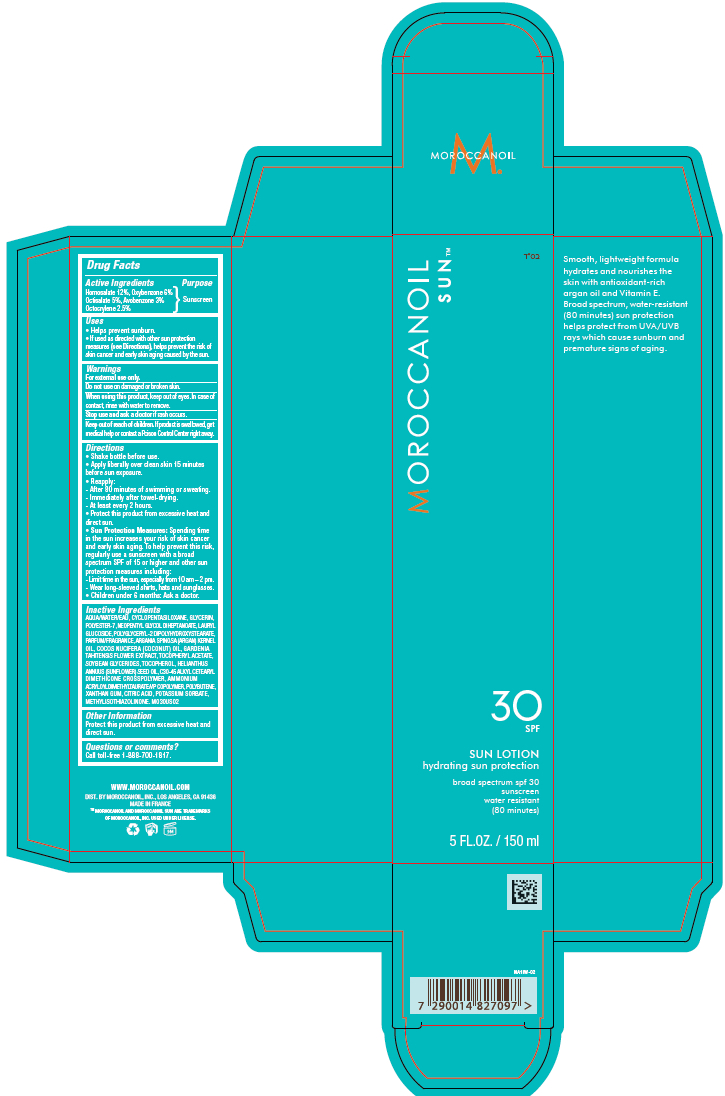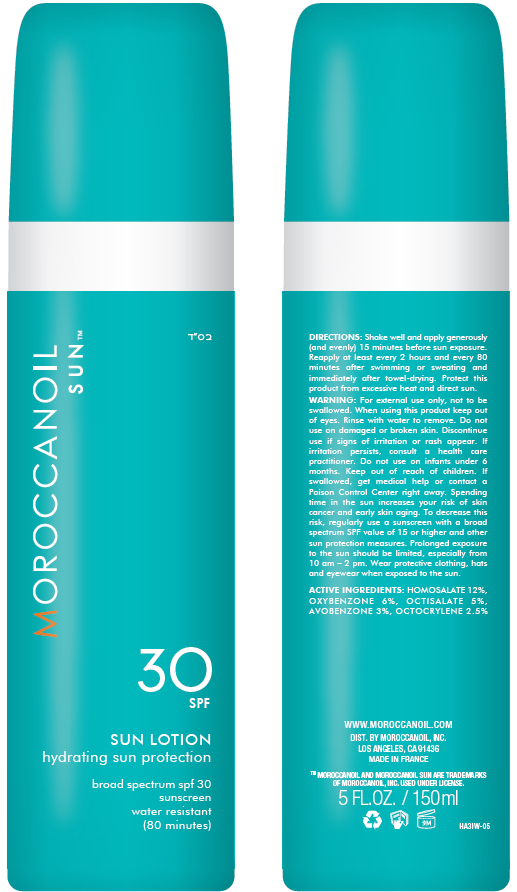 DRUG LABEL: Moroccanoil SPF 30
NDC: 69942-030 | Form: LOTION
Manufacturer: Moroccanoil, Inc.
Category: otc | Type: HUMAN OTC DRUG LABEL
Date: 20201215

ACTIVE INGREDIENTS: HOMOSALATE 12 g/100 mL; OCTISALATE 5 g/100 mL; OXYBENZONE 6 g/100 mL; OCTOCRYLENE 2.5 g/100 mL; AVOBENZONE 3 g/100 mL
INACTIVE INGREDIENTS: CYCLOMETHICONE 5; GARDENIA TAITENSIS FLOWER; GLYCERIN; LAURYL GLUCOSIDE; NEOPENTYL GLYCOL DIHEPTANOATE; POLYBUTENE (1400 MW); POTASSIUM SORBATE; AMMONIUM ACRYLOYLDIMETHYLTAURATE/VP COPOLYMER; CITRIC ACID MONOHYDRATE; COCONUT OIL; METHYLISOTHIAZOLINONE; POLYESTER-7; POLYGLYCERYL-2 DIPOLYHYDROXYSTEARATE; .ALPHA.-TOCOPHEROL ACETATE, D-; WATER; XANTHAN GUM; HELIANTHUS ANNUUS SEED WAX; SOYBEAN OIL

Moroccanoil Sun Lotion SPF 30

PURPOSE

Sunscreen

ACTIVE INGREDIENTS

Avobenzone 3%, Homosalate 12%
Octisalate 5%, Octocrylene 2.5%
Oxybenzone%

Avobenzone 3%

Homosalate 12%

Octisalate 5%

Octocrylene 2.5%

Oxybenzone 6%

USES

Helps prevent sunburn.

If used as directed with other sun protection measures (see Directions), helps prevent the risk of skin cancer and early skin aging caused by the sun.

DIRECTIONS

Shake bottle before use.

Apply liberally over clean skin 15 minutes before sun exposure.

Reapply:

-- After 80 minutes of swimming or sweating.

-- Immediately after towel-drying.

-- At least every 2 hours.

Protect this product from excessive heat and direct sun.

Sun Protection Measures: Spending time in the sun increases your risk of skin cancer and early skin aging. To help prevent this risk, regularly use a sunscreen with a broad spectrum SPF of 15 or higher and other sun protection measures including:

-- Limit time in the sun, especially from 10 am – 2 pm.

-- Wear long-sleeved shirts, hats and sunglasses.

Children under 6 months: Ask a doctor.

KEEP OUT OF REACH OF CHILDREN

WARNINGS

For external use only.

Do not use on damaged or broken skin.

When using this product, keep out of eyes. In case of contact, rinse with water to remove.

Stop use and ask a doctor if rash occurs.

Keep out of reach of children. If product is swallowed, get medical help or contact a Poison Control Center right a way.

INACTIVE INGREDIENTS

AQUA (WATER), C12-15 ALKYL BENZOATE, BUTYLOCTYL SALICYLATE, GLYCERIN, CYCLOPENTASILOXANE, POLYESTER-7, HYDROGENATED DIMER DILINOLEYL/DIMETHYLCARBONATE COPOLYMER, NEOPENTYL GLYCOL DIHEPTANOATE, DIMETHICONE, TRIMETHYLSILOXYSILICATE, PARFUM (FRAGRANCE), ARGANIA SPINOSA KERNEL OIL, BENZOTRIAZOLYL DODECYL P-CRESOL, COCOS NUCIFERA (COCONUT) OIL, TOCOPHERYL ACETATE, SOYBEAN GLYCERIDES, GARDENIA TAHITENSIS FLOWER EXTRACT, TOCOPHEROL, HELIANTHUS ANNUUS (SUNFLOWER) SEED OIL, LAURYL GLUCOSIDE, POLYGLYCERYL-2 DIPOLYHYDROXYSTEARATE, C30-45 ALKYL CETEARYL DIMETHICONE CROSSPOLYMER, POLYBUTENE, XANTHAN GUM, CITRIC ACID, POTASSIUM SORBATE, METHYLISOTHIAZOLINONE.

QUESTIONS OR COMMENTS?

Call toll-free 1-888-700-1817

PACKAGING

Product Bottle Label

Product Box Label